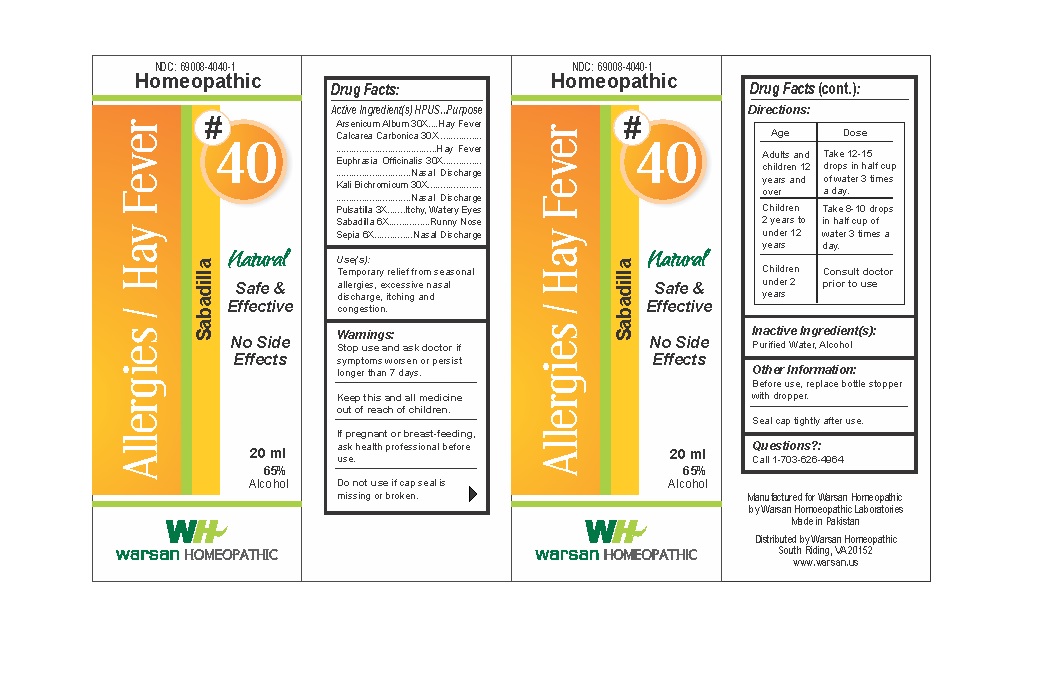 DRUG LABEL: Combination Remedy 40 - Allergies Hay Fever
NDC: 69008-4040 | Form: SOLUTION/ DROPS
Manufacturer: Warsan Homoeopathic Laboratories
Category: homeopathic | Type: HUMAN OTC DRUG LABEL
Date: 20171225

ACTIVE INGREDIENTS: EUPHRASIA STRICTA 30 [hp_X]/1 mL; POTASSIUM DICHROMATE 30 [hp_X]/1 mL; ARSENIC TRIOXIDE 30 [hp_X]/1 mL; SCHOENOCAULON OFFICINALE SEED 6 [hp_X]/1 mL; SEPIA OFFICINALIS JUICE 6 [hp_X]/1 mL; OYSTER SHELL CALCIUM CARBONATE, CRUDE 30 [hp_X]/1 mL; PULSATILLA VULGARIS 3 [hp_X]/1 mL
INACTIVE INGREDIENTS: ALCOHOL; WATER

Stop use and ask doctor if symptoms worsen or persist longer than 7 days.

If pregnant or breast-feeding, ask health professional before use.

Do not use if tamper evident seal is missing or broken.

Keep out of reach of children.

ACTIVE INGREDIENT

Arsenicum Album 30X

Calcarea Carbonica 30X

Euphrasia Officinalis 30X

Kali Bichromicum 30X

Pulsatilla 3X

Sabadilla 6X

Sepia 6X

PURPOSE

Temporary relief from seasonal allergies, excessive nasal discharge, itching and congestion.

INACTIVE INGREDIENT

Purified Water

Alcohol

DOSAGE AND ADMINISTRATION

Adults and children 12 years and older: Take 10-15 drops in half cup of water 3 times a day.

Children 2 years to under 12 years: Take 8-10 drops in half cup of water of 3 times a day.

Children under 2 years: Consult doctor prior to use.

INDICATIONS AND USAGE

Temporary relief from seasonal allergies, excessive nasal discharge, itching and congestion.